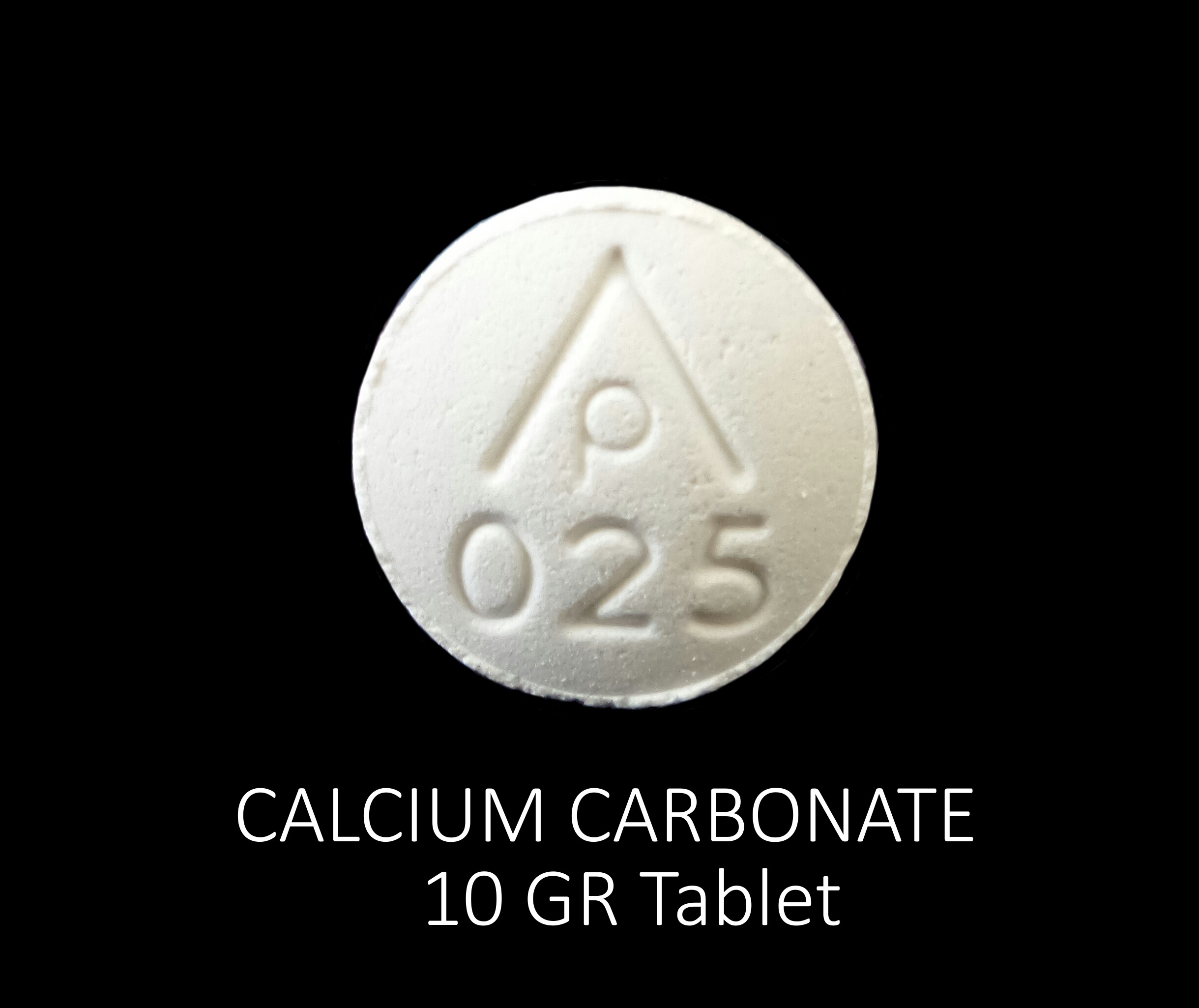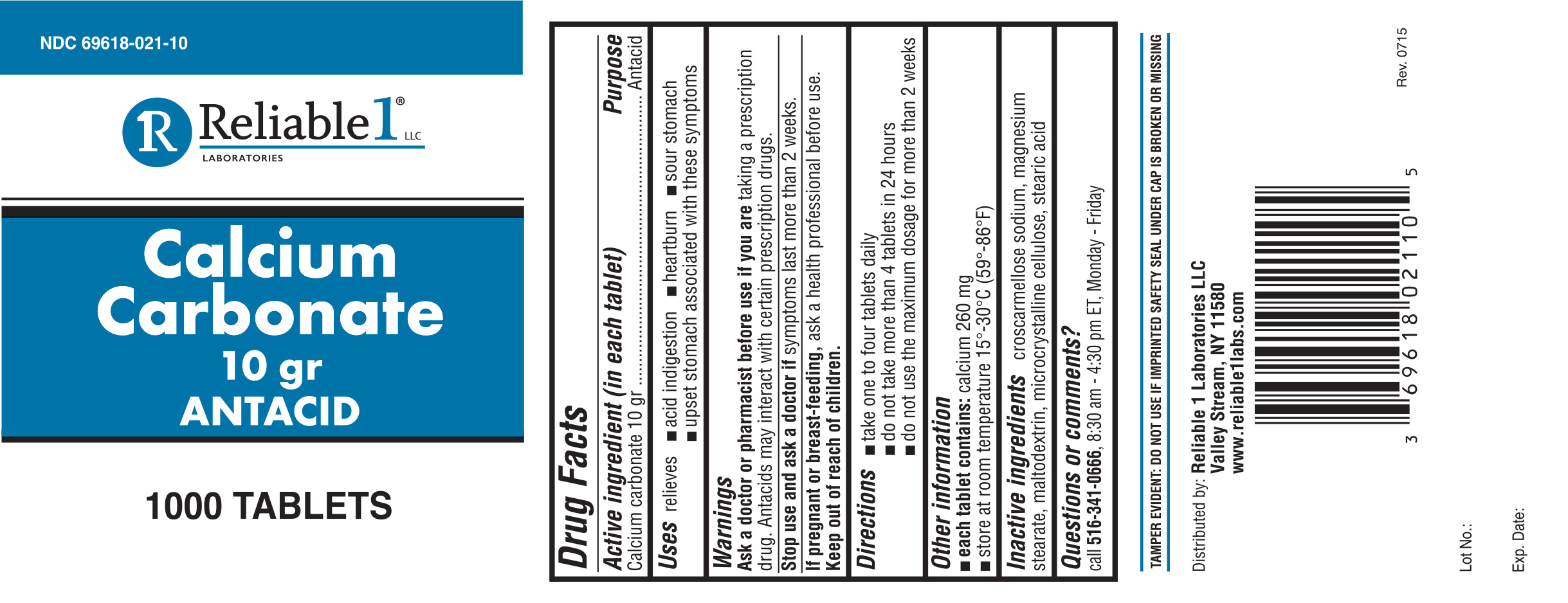 DRUG LABEL: Calsium Carbonate 10 gr
NDC: 69618-021 | Form: TABLET
Manufacturer: Reliable 1 Laboratories LLC
Category: otc | Type: HUMAN OTC DRUG LABEL
Date: 20211027

ACTIVE INGREDIENTS: CALCIUM CARBONATE 648 mg/1 1
INACTIVE INGREDIENTS: CROSCARMELLOSE SODIUM; MAGNESIUM STEARATE; STEARIC ACID; MALTODEXTRIN; CELLULOSE, MICROCRYSTALLINE

Reliable-1 Calcium Carbonate 10 gr

Active ingredient (in each tablet)

Calcium carbonate 10 gr

Purpose

Antacid

Uses

relieves

- acid indigestion
- heartburn
- sour stomach
- upset stomach associated with these symptoms

Warnings

Ask a doctor or pharmacist before use if you are taking a prescription drug. Antacids may interact with certain prescription drugs.

Stop use and ask a doctor if symptoms last more than 2 weeks.

If pregnant or breast-feeding, ask a health professional before use.

Keep out of reach of children.

Ask a doctor or pharmacist before use if you are taking a prescription drug. Antacids may interact with certain prescription drugs.

Stop use and ask a doctor if symptoms last more than 2 weeks.

PREGNANCY OR BREAST FEEDING

If pregnant or breast-feeding, ask a health professional before use.

Keep out of reach of children

Directions

- take one to four tablets daily
- do not take more than 4 tablets in 23 hours
- do not use the maximun dosage for more than 2 weeks

Other information

- each tablet contains: calcium 260 mg
- store at room temperature 15°-30°C (59°-86°F)

Inactive ingredients

croscarmellose sodium, magnesium stearate, maltodextrin, microcrystalline cellulose, stearic acid

Question or comments?

call 516-341-0666, 8:30 am - 4:30 pm ET, Monday - Friday

TAMPER EVIDENT: DO NOT USE IF IMPRINTED SAFETY SEAL UNDER CAP IS BROKEN OR MISSING

Distributed by: Reliable 1 Laboratories LLC

Valley Stream, NY 11580

www.reliable1labs.com

PACKAGE LABEL

NDC 69618-021-10

Calcium Carbonate 10 gr

ANTACID

1000 TABLETS